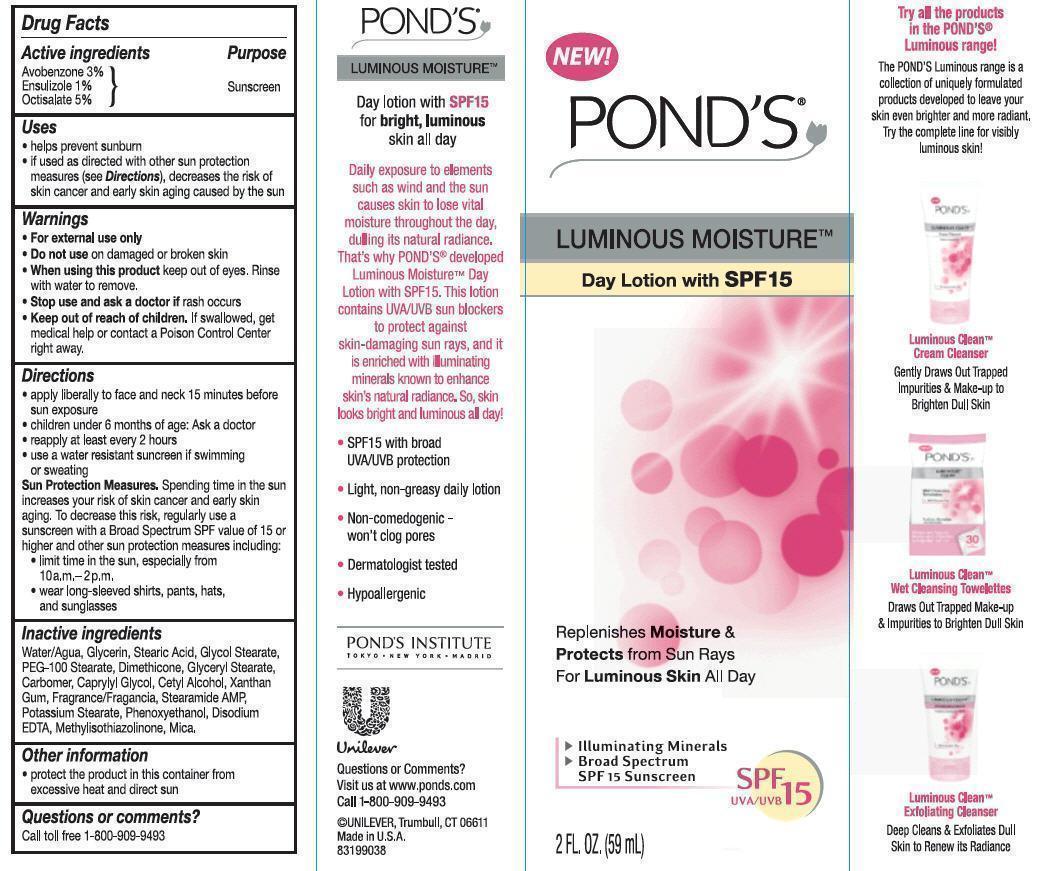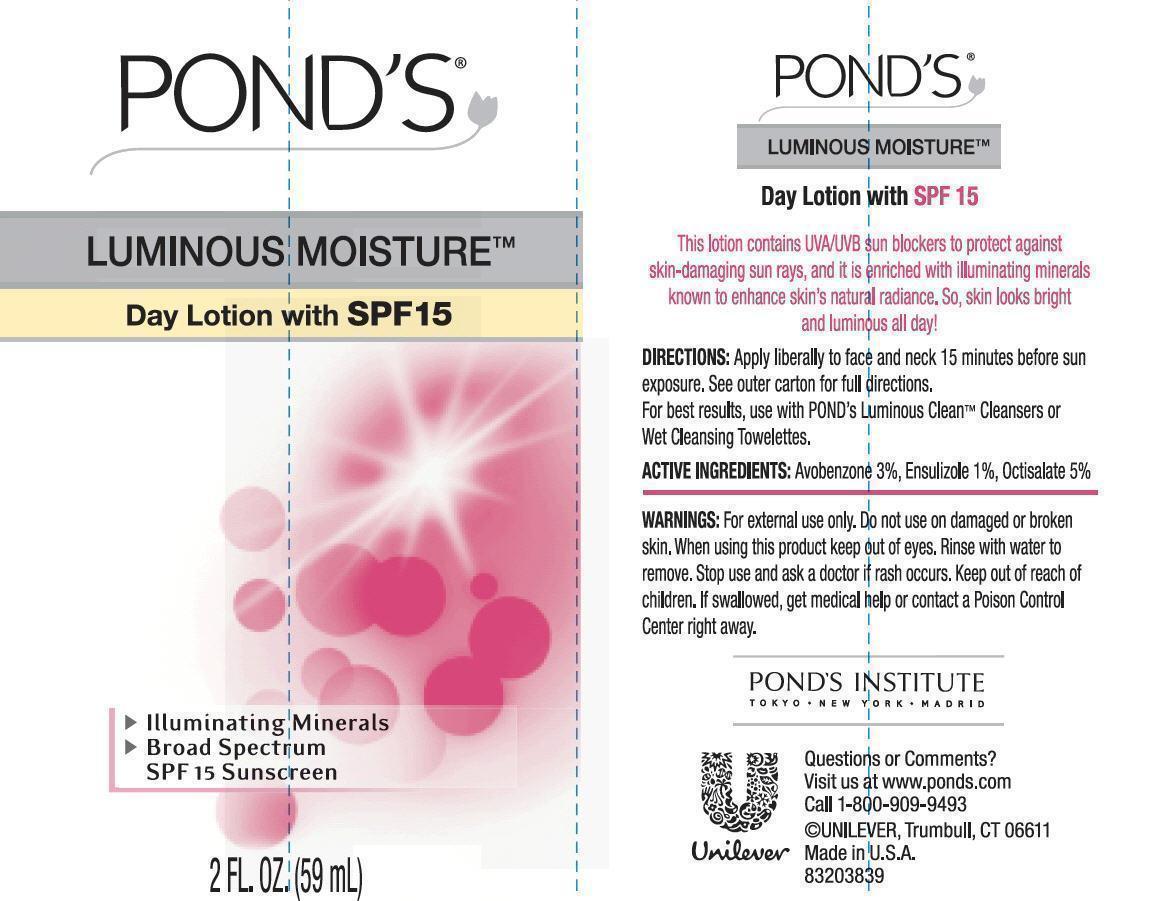 DRUG LABEL: Ponds
NDC: 64942-1288 | Form: LOTION
Manufacturer: CONOPCO Inc. d/b/a Unilever
Category: otc | Type: HUMAN OTC DRUG LABEL
Date: 20130130

ACTIVE INGREDIENTS: AVOBENZONE 3.0 g/100 mL; ENSULIZOLE 1.0 g/100 mL; OCTISALATE 5.0 g/100 mL
INACTIVE INGREDIENTS: WATER; GLYCERIN; STEARIC ACID; GLYCOL STEARATE; PEG-100 STEARATE; DIMETHICONE; METHYLISOTHIAZOLINONE; POTASSIUM STEARATE; GLYCERYL MONOSTEARATE; CAPRYLYL GLYCOL; CETYL ALCOHOL; XANTHAN GUM; STEARAMIDE AMP; MICA; PHENOXYETHANOL; EDETATE DISODIUM

Pond's Luminous Moisture Day Lotion SPF 15

Active Ingredients
AVOBENZONE (3.0%)
ENSULIZOLE (1.0%)
OCTISALATE (5.0%)

Purpose
Sunscreen

Uses
· helps prevent sunburn
· if used as directed with other sun protection measures (see Directions), decreases the risk of skin cancer and early skin aging caused by the sun

Warnings
· For external use only.

· Do not use on damaged or broken skin.

· When using this product keep out of eyes. Rinse with water to remove.

· Stop use and ask a doctor if rash occurs.

· Keep out of reach of children. If swallowed, get medical help or contact a Poison Control Center right away.

Directions
· apply liberally to face and neck 15 minutes before sun exposure
· children under 6 months of age: Ask a doctor
· reapply at least every 2 hours
· use a water resistant sunscreen if swimming or sweating
Sun Protection Measures. Spending time in the sun increases your risk of skin cancer and early skin aging. To decrease this risk, regularly use a sunscreen with a Broad Spectrum SPF value of 15 or higher and other sun protection measures including:
· limit time in the sun, especially from 10a.m. - 2p.m.
· wear long-sleeved shirts, pants, hats, and sunglasses

Inactive ingredients
Water/Agua
Glycerin
Stearic Acid
Glycol Stearate
PEG-100 Stearate
Dimethicone
Glyceryl Stearate
Carbomer
Caprylyl Glycol
Cetyl Alcohol
Xanthan Gum
Fragrance/Fragancia
Stearamide AMP
Potassium Stearate
Phenoxyethanol
Disodium EDTA
Methylisothiazolinone
Mica

Questions or comments?
Call toll free 1-800-909-9493

PACKAGE LABEL

PDP

PACKAGE LABEL

Carton